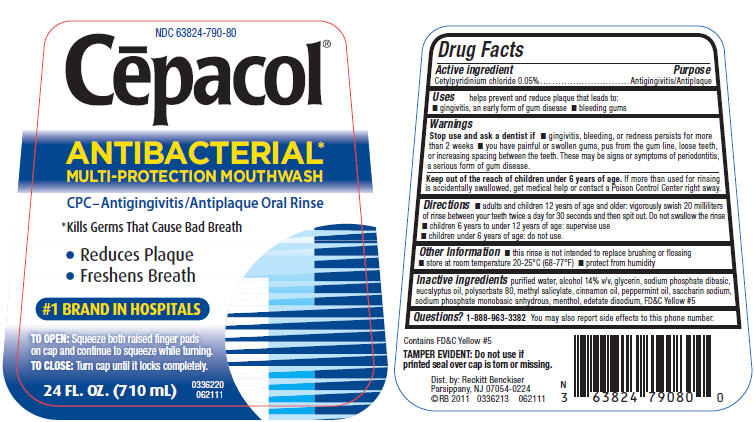 DRUG LABEL: Cepacol
NDC: 63824-790 | Form: LIQUID
Manufacturer: RB Health (US) LLC
Category: otc | Type: HUMAN OTC DRUG LABEL
Date: 20251223

ACTIVE INGREDIENTS: CETYLPYRIDINIUM CHLORIDE 0.05 g/100 mL
INACTIVE INGREDIENTS: WATER; ALCOHOL; GLYCERIN; SODIUM PHOSPHATE, DIBASIC, UNSPECIFIED FORM; EUCALYPTUS OIL; POLYSORBATE 80; METHYL SALICYLATE; CINNAMON OIL; PEPPERMINT OIL; SACCHARIN SODIUM; SODIUM PHOSPHATE, MONOBASIC, ANHYDROUS; MENTHOL, UNSPECIFIED FORM; EDETATE DISODIUM; FD&C YELLOW NO. 5

Cēpacol®
ANTIBACTERIAL
MULTI-PROTECTION MOUTHWASH

Drug Facts

Active ingredient

Cetylpyridinium chloride 0.05%

Purpose

Antigingivitis/Antiplaque

Uses

helps prevent and reduce plaque that leads to:

- gingivitis, an early form of gum disease
- bleeding gums

Warnings

Stop use and ask a dentist if

- gingivitis, bleeding, or redness persists for more than 2 weeks
- you have painful or swollen gums, pus from the gum line, loose teeth, or increasing spacing between the teeth. These may be signs or symptoms of periodontitis, a serious form of gum disease.

KEEP OUT OF REACH OF CHILDREN

Keep out of the reach of children under 6 years of age.If more than used for rinsing is accidentally swallowed, get medical help or contact a Poison Control Center right away.

Directions

- adults and children 12 years of age and older: vigorously swish 20 milliliters of rinse between your teeth twice a day for 30 seconds and then spit out. Do not swallow the rinse
- children 6 years to under 12 years of age: supervise use
- children under 6 years of age: do not use.

Other Information

- this rinse is not intended to replace brushing or flossing
- store at room temperature 20-25°C (68-77°F)
- protect from humidity

Inactive ingredients

purified water, alcohol 14% v/v, glycerin, sodium phosphate dibasic, eucalyptus oil, polysorbate 80, methyl salicylate, cinnamon oil, peppermint oil, saccharin sodium, sodium phosphate monobasic anhydrous, menthol, edetate disodium, FD&C Yellow #5

Questions?

1-888-963-3382You may also report side effects to this phone number.

Dist. by: Reckitt Benckiser
Parsippany, NJ 07054-0224

PRINCIPAL DISPLAY PANEL - 710 mL Bottle Label

NDC 63824-790-80

Cēpacol®

ANTIBACTERIAL*
MULTI-PROTECTION MOUTHWASH

CPC–Antigingivitis/Antiplaque Oral Rinse

*Kills Germs That Cause Bad Breath

- Reduces Plaque
- Freshens Breath

#1 BRAND IN HOSPITALS

TO OPEN:Squeeze both raised finger pads
on cap and continue to squeeze while turning.

TO CLOSE:Turn cap until it locks completely.

24 FL. OZ. (710 mL)

0336220
062111